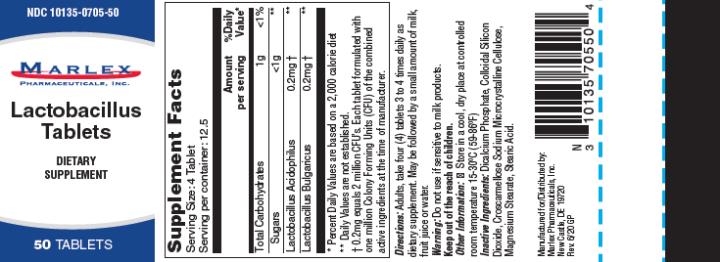 DRUG LABEL: Lactobacillus
NDC: 10135-705 | Form: TABLET
Manufacturer: Marlex Pharmaceuticals Inc
Category: other | Type: DIETARY SUPPLEMENT
Date: 20201006

ACTIVE INGREDIENTS: LACTOBACILLUS ACIDOPHILUS 0.2 mg/1 1; LACTOBACILLUS DELBRUECKII BULGARICUS 0.2 mg/1 1
INACTIVE INGREDIENTS: CALCIUM PHOSPHATE, DIBASIC, ANHYDROUS; SILICON DIOXIDE; CROSCARMELLOSE SODIUM; MICROCRYSTALLINE CELLULOSE; MAGNESIUM STEARATE; STEARIC ACID

Lactobacillus Tablets

Supplement Facts

Serving Size: 4 Tablet
Serving per container: 12.5
 | Amount Per serving | % Daily Value*
Total Carbohydrates | 1g | <1 %
Sugars | <1g | **
Lactobacillus Acidophilus | 0.2mg Ϯ | **
Lactobacillus Bulgaricus | 0.2mg Ϯ | **

Lactobacillus Tablets

*Percent Daily Values are based on a 2,000 Calorie Diet

** Daily Values are not established

Ϯ 0.2mg equals 2 million CFU’s. Each tablet formulated with one million Colony Forming Units (CFU) of the combined active ingredients at the time of manufacturer.

Directions:

Adults, take four (4) tablets 3 to 4 times daily as dietary supplement. May be followed by a small amount of milk, fruit juice or water.

Warnings:

Do not use if sensitive to milk products.

Keep out of the reach of children.

Other Information:

Store in a cool, dry place at controlled room temperature 15-30°C (59-86°F)

Inactive Ingredients:

Dicalcium Phosphate, Colloidal Silicon Dioxide, Croscarmellose Sodium, Microcrystalline Cellulose, Magnesium Stearate, Stearic Acid.

PRINCIPAL DISPLAY PANEL

Manufactured for/ Distributed by:

Marlex Pharmaceuticals, Inc.

New Castle, DE 19720

Rev. 6/20 GP